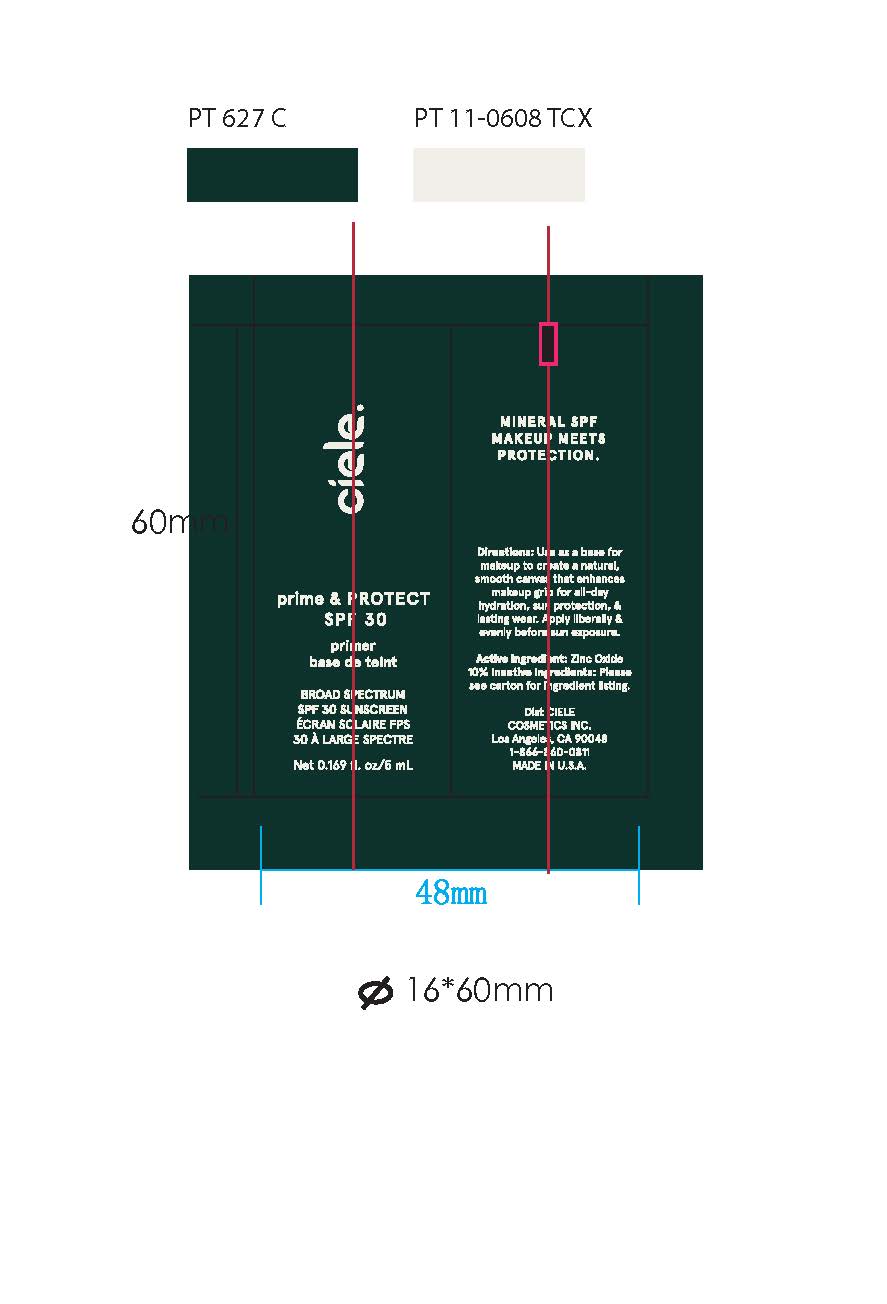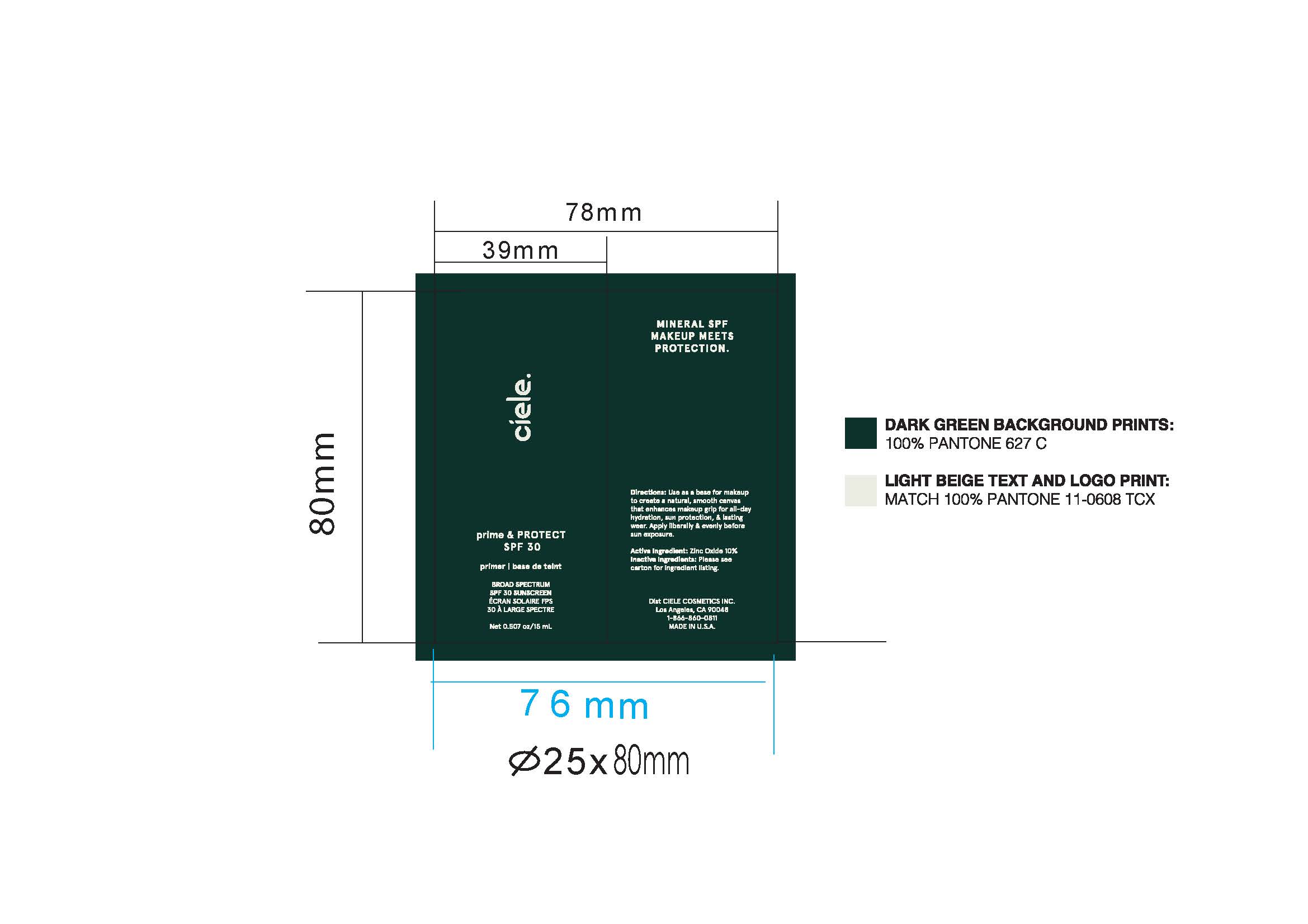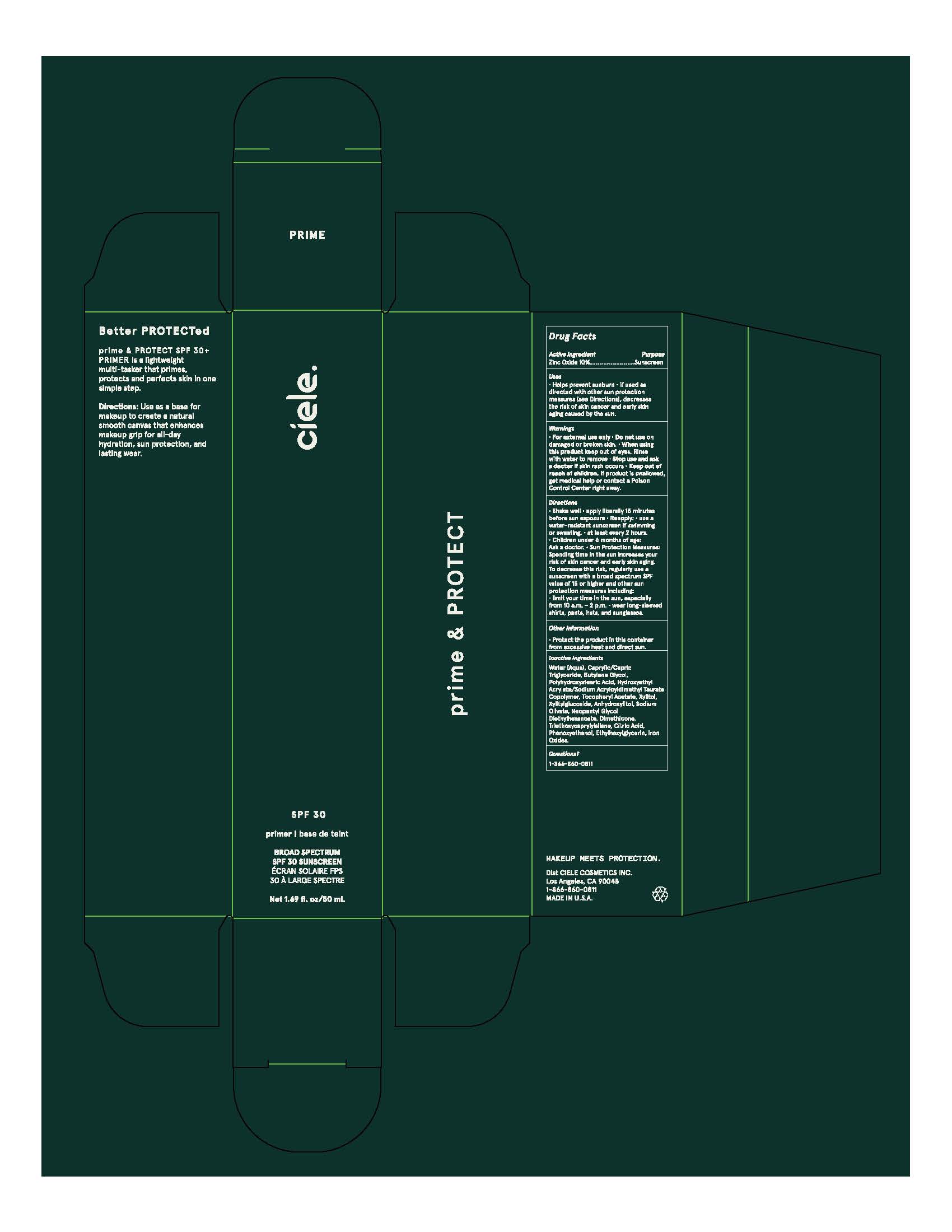 DRUG LABEL: Ceile SPF 30 prime PROTECT Broad Spectrum SPF 30 Sunscreen
NDC: 83103-2000 | Form: CREAM
Manufacturer: LÚE COSMETICS INC
Category: otc | Type: HUMAN OTC DRUG LABEL
Date: 20260125

ACTIVE INGREDIENTS: ZINC OXIDE 10 mg/100 mg
INACTIVE INGREDIENTS: WATER; CAPRYLIC/CAPRIC TRIGLYCERIDE; BUTYLENE GLYCOL; POLYHYDROXYSTEARIC ACID (2300 MW); HYDROXYETHYL ACRYLATE/SODIUM ACRYLOYLDIMETHYL TAURATE COPOLYMER (45000 MPA.S AT 1%); XYLITOL; XYLITYLGLUCOSIDE; ANHYDROXYLITOL; SODIUM OLIVATE; NEOPENTYL GLYCOL DIETHYLHEXANOATE; DIMETHICONE; TRIETHOXYCAPRYLYLSILANE; CITRIC ACID; PHENOXYETHANOL; ETHYLHEXYLGLYCERIN; BROWN IRON OXIDE

DRUG FACTS

Active Ingredients

Zinc Oxide 10.00%

Uses

● helps prevent sunburn
● if used as directed with other sun protection measures (see Directions),
decreases the risk of skin cancer and early skin aging caused by the sun

Warnings

For external use only
Do not use on damaged or broken skin.
When using this product keep out of eyes. Rinse with water to remove.
Stop use and ask a docor if rash occurs
Keep out of reach of children. If swallowed, get medical help or contact a Poison Control Center right away.

Directions

• Shake Well •apply generously 15 minutes before sun exposure and as needed
• reapply at least every 2 hours.

• use a water resistant sunscreen if swimming or sweating
• Sun Protection Measures. Spending time in the sun

increases your risk of skin cancer and early skin aging. To decrease
this risk, regularly use a sunscreen with a Broad Spectrum SPF
value of 15 or higher and other sun protection measures including:
• limit time in the sun, especially from 10 a.m. - 2 p.m.
• wear long-sleeved shirts, pants, hats, and sunglasses
• children under 6 months of age: Ask a doctor

Inactive ingredients

Water (Aqua), Caprylic/Capric Triglyceride, Butylene Glycol, Polyhydroxystearic Acid, Hydroxyethyl Acrylate/Sodium Acryloyldimethyl Taurate Copolymer, Tocopheryl Acetate, Xylitol, Xylitylglucoside, Anhydroxylitol, Sodium Olivate, Neopentyl Glycol Diethylhexanoate, Dimethicone, Triethoxycaprylylsilane, Citric Acid, Phenoxyethanol, Ethylhexylglycerin, Iron Oxides.

Other Information

Protect the product in this container from excessive heat and direct sun.

Questions?

1-866-860-0811

Purpose

Sunscreen

Purpose

Sunscreen

Keep out of reach of children